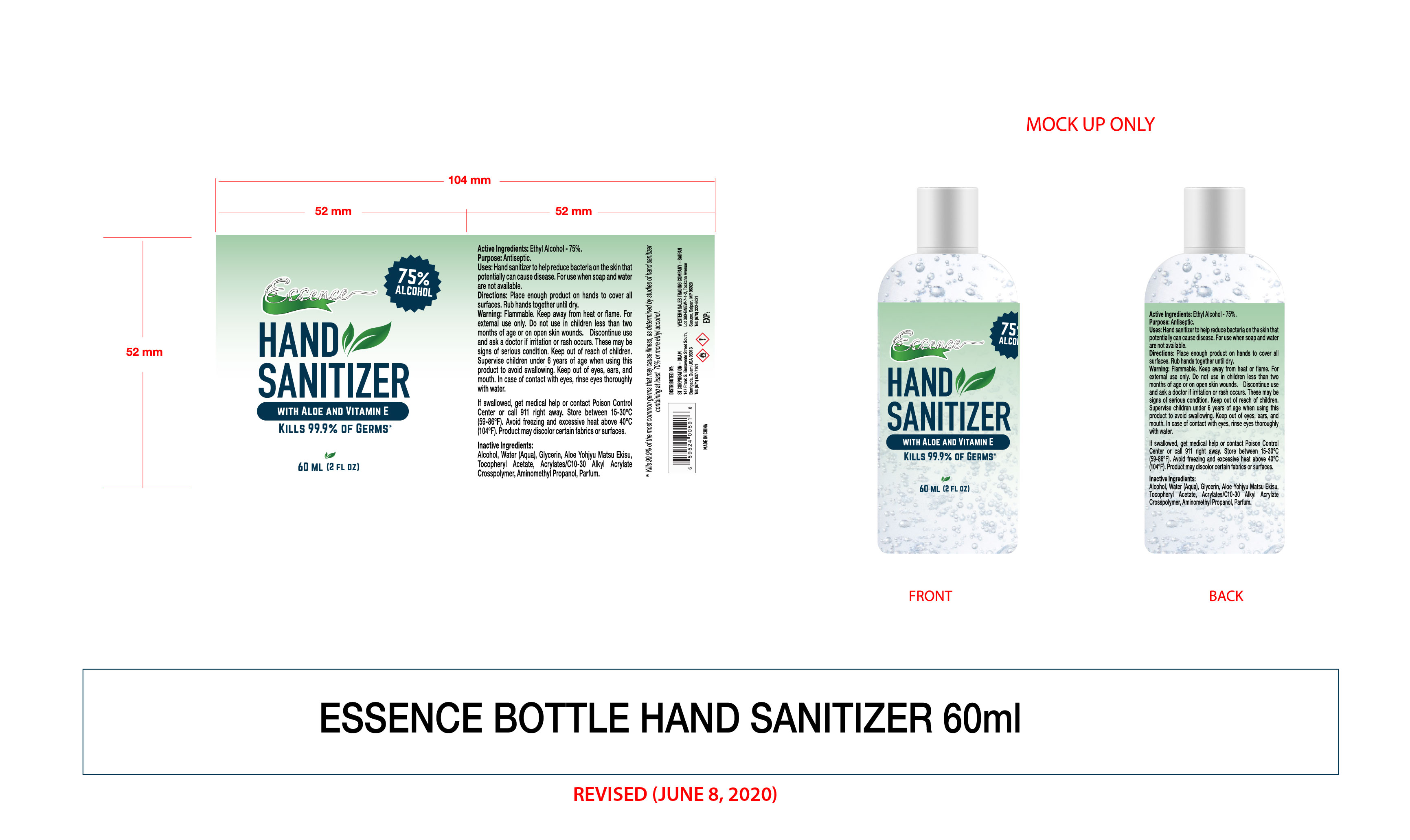 DRUG LABEL: ESSENCE hand sanitizer 60ML
NDC: 54860-324 | Form: LIQUID
Manufacturer: Shenzhen Lantern Scicence Co Ltd
Category: otc | Type: HUMAN OTC DRUG LABEL
Date: 20200811

ACTIVE INGREDIENTS: ALCOHOL 75 mL/100 mL
INACTIVE INGREDIENTS: ALOE ANDONGENSIS WHOLE 0.1 mL/100 mL; ALOE 0.1 mL/100 mL; CARBOMER INTERPOLYMER TYPE A (55000 CPS) 0.3 mL/100 mL; AMINOMETHYLPROPANOL 0.09 mL/100 mL; WATER 23.9 mL/100 mL; GLYCERIN 0.5 mL/100 mL; .ALPHA.-TOCOPHEROL ACETATE 0.01 mL/100 mL

ESSENCE hand sanitizer 60ML

Active ingredient

Active Ingredient Purpose

Ethyl Alcohol 75%（V/V） Antiseptic

USE

Hand sanitizer to help reduce bacteria on the skin that potentially can cause disease.For use when soap and water are not available.

DOSAGE AND ADMINISTRATION

Recommended for repeated use.

use anywhere without water.

Warning

Flammable,Keep away from heat or flame.For external use only.Do not use in children less than two months of age or on open skin wounds. Discontinue use and ask a doctor if irritation or rash occurs.These may be signs of serious condition.Keep out of reach of children.Supervise children under 6 years of age when using this product to avoid swallowing.Keep out of eyes,ears ,and mouth.In case of contact with eyes, rinse eyes thoroughly with water.

If swallowed, get medical help or contact Poison Control Center or call 911 right away.Store between 15-30℃（59-86℉）。Avoid freezing and excessive heat above 40℃（104℉）。Product may discolor certain fabrics or surfaces.

WARNINGS AND PRECAUTIONS

For external use only.

Flammable, keep away from heat and flame.

STOP USE

Discontinue if skin becomes irritated and ask a doctor .

Keep out of reach of children. In case of accidental ingestion, seek professional assistance or contact a poson control center immediately.

Inactive ingredients

Aqua,Glycerin,Aloe Yohjyu Matsu Ekisu,Tocopheryl Acetate,Acrylates/C10-30 Alkyl Acrylate Crosspolymer,Aminomethyl Propanol,Parfum.

Directions

Place enough product on hands to cover all surfaces.Rub hands together until dry.

When using this product

keep out of eyes. In case of contact with eyes, flush thoroughly with water.

Do not inhale or ingest.

Avoid contact with broken skin.

Other information

Do not store above 105F.

May discolor some fabrics.

Harmful to wood finishes and plastics.